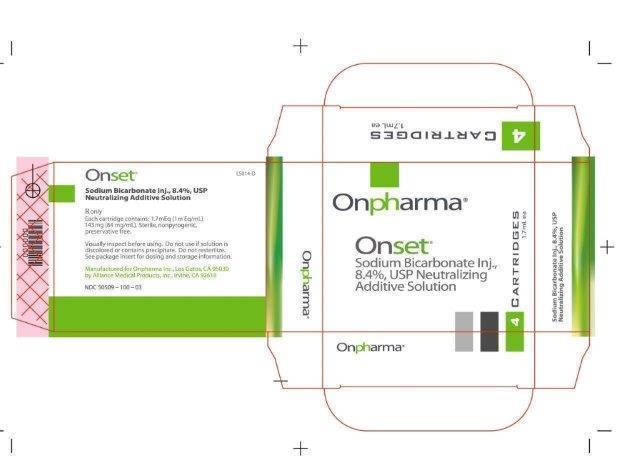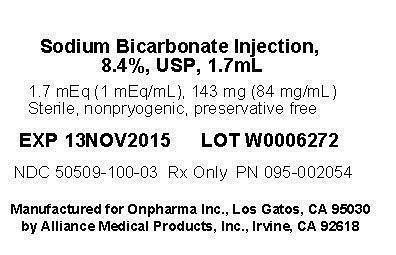 DRUG LABEL: Sodium Bicarbonate
NDC: 50509-100 | Form: SOLUTION
Manufacturer: Onpharma, Inc.
Category: prescription | Type: HUMAN PRESCRIPTION DRUG LABEL
Date: 20140131

ACTIVE INGREDIENTS: SODIUM BICARBONATE 84 mg/1 mL

SODIUM BICARBONATE INJ., 8.4% USP NEUTRALIZING ADDITIVE SOLUTION Rx only Volume 2.7 mL per cartridge 2.7 mEq (1mEq/mL) Volume 1.7 mL per cartridge 1.7 mEq (1mEq/mL)

DESCRIPTION:

Sodium Bicarbonate Inj., 8.4% USP Neutralizing Additive Solution is a sterile, nonpyrogenic, solution of sodium bicarbonate (NaHCO3) in Water for Injection. It is added to an appropriate local anesthetic as a neutralizing agent immediately prior to administration.

The solution contains no bacteriostat, antimicrobial agent or added buffer and is intended only for single-use. pH is adjusted with carbon dioxide. Per the USP monograph for Sodium Bicarbonate Inj., pH is between 7.0 and 8.5. Osmolar concentration is 2 mOsmol/mL (calc.).

Sodium bicarbonate, 84 mg is equal to one milliequivalent each of Na+ and HCO3-.

Sodium Bicarbonate, USP is chemically designated as NaHC03, a white crystalline powder soluble in water. Sodium bicarbonate in water dissociates to provide sodium (Na+) and bicarbonate (HCO3-) ions.

Sodium (Na+) is the principal cation of the extracellular fluid and plays a large part in the therapy of fluid and electrolyte disturbances. Bicarbonate (HCO3-) is a normal constituent of body fluids and the normal plasma level ranges from 24 to 31 mEq/liter. Bicarbonate anion is considered “labile” since at a proper concentration of hydrogen ion (H+) it may be converted to carbonic acid (H2CO3) and thence to its volatile form, carbon dioxide (CO2) excreted by the lung. Normally a ratio of 1:20 (carbonic acid; bicarbonate) is present in the extracellular fluid. In a healthy adult with normal kidney function, practically all the glomerular filtered bicarbonate ion is reabsorbed; less than 1% is excreted in the urine.

Non-neutral parenteral solutions with a low (acidic) pH are known to cause chemical irritation of tissues.

INDICATIONS AND USAGE:

Sodium Bicarbonate Inj., 8.4% USP Neutralizing Additive Solution is indicated to hasten onset of analgesia and reduce injection pain, by adjusting commercial preparations of Lidocaine w/ Epinephrine anesthetic solution to a more physiologic pH.

DOSAGE AND ADMINISTRATION

The practitioner should choose a volume of Sodium Bicarbonate Inj., 8.4% USP Neutralizing Additive Solution to be mixed with Lidocaine w/ Epinephrine in a ratio of 1:10 (local anesthetic solution to sodium bicarbonate solution).
The below table provides a mixing guide showing for convenience the volumes of 8.4% Sodium Bicarbonate Neutralizing Additive Solution to be added to the commercial preparations of Lidocaine with Epinephrine in order to achieve a mixed ratio of 10:1.

10:1 Anesthetic-to-Bicarbonate Solution Ratio Mixing Guide for 10:1

Volume (mL), Lidocaine w/ Epinephrine (container type) | Volume (mL), 8.4% Sodium Bicarbonate Solution
1.8 mL (cartridge) | 0.18 mL
20 mL (Vial) | 2.0 mL
30 mL (Vial) | 3.0 mL
50 mL (Vial) | 5.0 m

CONTRAINDICATIONS:

Not for use as a systemic alkalizer.

WARNINGS:

None known.

PRECAUTIONS:

Administer local anesthetic solution immediately after combining with Sodium Bicarbonate Inj., 8.4% USP Neutralizing Additive Solution.
When combining local anesthetic solution with Sodium Bicarbonate Inj., 8.4% USP Neutralizing Additive Solution, use aseptic technique, mix thoroughly, and do not store.
Do not use unless Sodium Bicarbonate Inj., 8.4% USP Neutralizing Additive Solution is clear, colorless, and free of particulates or cloudiness, and the container or seal is intact. Do not use if the inner or outer packaging are damaged. Discard unused portion.

Do not use local anesthetic combined with Sodium Bicarbonate Inj., 8.4% USP Neutralizing Additive Solution unless the combined solution is clear, colorless, and free of particulates or cloudiness.

Parenteral drug products should be inspected visually for particulate matter, cloudiness and discoloration prior to administration, whenever solution and container permit.

Drug Interactions

Sodium Bicarbonate Inj., 8.4% USP Neutralizing Additive Solution and Lidocaine w/ Epinephrine are compatible. See Compatibility section under Sodium Bicarbonate in The Handbook on Injectable Drugs by Lawrence A. Trissel, 14th ed. 2007 (American Society of Health-System Pharmacists, Bethesda, MD).

Pregnancy Category C

Animal reproduction studies have not been conducted in which Sodium Bicarbonate Inj., 8.4% USP Neutralizing Additive Solution was evaluated. Animal reproduction studies have not been conducted in which Lidocaine w/ Epinephrine that has been pH adjusted by the addition of Sodium Bicarbonate Inj., 8.4% USP Neutralizing Additive Solution was evaluated.

It is not known whether Sodium Bicarbonate Inj., 8.4% USP Neutralizing Additive Solution can cause fetal harm when administered to a pregnant woman or whether it can affect reproduction capacity. It is not known whether Lidocaine w/ Epinephrine that has been pH adjusted by the addition of Sodium Bicarbonate Inj., 8.4% USP Neutralizing Additive Solution can cause fetal harm when administered to a pregnant woman or whether it can affect reproduction capacity.

ADVERSE REACTIONS:

None known.

OVERDOSAGE:

Adding a volume of Sodium Bicarbonate Inj., 8.4% USP Neutralizing Additive Solution to Lidocaine w/ Epinephrine solution such that the pH of the Lidocaine w/ Epinephrine is raised above physiologic pH may cause anesthetic to precipitate out of solution, reducing the clinical effectiveness of the anesthetic. See, e.g., Mulroy MF, Regional Anesthesia, An Illustrated Procedural Guide, 3rd Ed. 2002 (Lippincott Williams and Wilkins, Philadelphia, PA). In addition, solutions that contain precipitate should not be injected.
Adding a volume of Sodium Bicarbonate Inj., 8.4% USP Neutralizing Additive Solution to Lidocaine w/ Epinephrine solution such that the pH of the Lidocaine w/ Epinephrine is raised well above (7.8) physiologic pH may cause tissue irritation when the solution is injected. See Whitcomb M, et al, A Prospective Randomized, Double Blind Study of the Anesthetic Efficacy of Sodium Bicarbonate Buffered 2% Lidocaine with 1:100,000 Epinephrine in Inferior Alveolar Nerve Blocks, Anesth Prog, vol 57, p 59 (2010).

HOW SUPPLIED:

Sodium Bicarbonate Inj., 8.4% USP is supplied in 2.7 mL or 1.7 mL single-dose cartridges, packaged in a four-cartridge package.

STORAGE AND HANDLING

Store at 20°-25°C (68°-77°F). (See USP).

REFERENCES, INDICATIONS AND USAGE:

Barash PG, Cullen BF, Stoelting RK, Clinical Anesthesia (4th Ed. 2001 Lippincott Williams and Wilken).
Bhatt H, Powell KJ, Jean DA, First Aid for the Anesthesiology Boards, An Insider's Guide (2011, McGraw-Hill Medical).
Cepeda MS, Tzortzopoulou A, Thackrey M, Hudcova J, Arora Gandhi P, Schumann R., Adjusting the pH of lidocaine for reducing pain on injection. Cochrane Database of Systematic Reviews 2010, Issue 12. Art. No.: CD006581.
Chu LF, Clinical Anesthesiology Board Review(2005, McGraw-Hill Medical).
Malamed SF,Handbook of Local Anesthesiology(5th Ed. 2004, Elsevier Mosby).
Miller RD, Miller's Anesthesia (6th Ed. 2004).
Stoelting RK, Miller RD,Basics of Anesthesia(5th Ed. 2007, Churchill Livingstone Elsevier).

REFERENCES, DOSAGE:

Christoph RA, Buchanan L, Begalla K, Schwartz S, Pain reduction in local anesthetic administration through pH buffering, Annals of Emergency Medicine, vol 17, no 2, p 117 (1988).

Martin AJ, pH-adjustment and discomfort caused by the intradermal injection of lignocaine, Anaesthesia, vol 45, p 975 (1990).

Masters JE, Randomised control trial of pH buffered lignocaine with adrenaline in outpatient operations, British Journal of Plastic Surgery, vol 51, p 385 (1998).

McKay W, Morris R, Mushlin P, Sodium bicarbonate attenuates pain on skin infiltration with or without epinephrine, Anesthesia and Analgesia, vol 66, p 572 (1987).

Narvaez J, Wessels I, Bacon G, Chin VR, Baqai WK, Zimmerman GJ, Prospective randomized evaluation of short-term complications when using buffered or unbuffered lidocaine 1% with epinephrine for blepharoplasty surgery, Ophthalmic Plastic and Reconstructive Surgery, vol 26, no1, p 33 (2010).

Talu H, Elibol O, Yanyali A, Karabas L, Alp B, Caglar Y, Effect of warming and buffering lidocaine on pain during facial anesthesia, Annals of Ophthalmology, vol 33, no 1, p 43 (2001).

Manufactured for Onpharma Inc., Los Gatos, CA 95030

Customer Care Center: (877) 336-6738
NDC 50509-100-01
NDC 50509-100-03
Copyright © 2011 Onpharma Inc. All Rights Reserved (11/2011) LS013-D